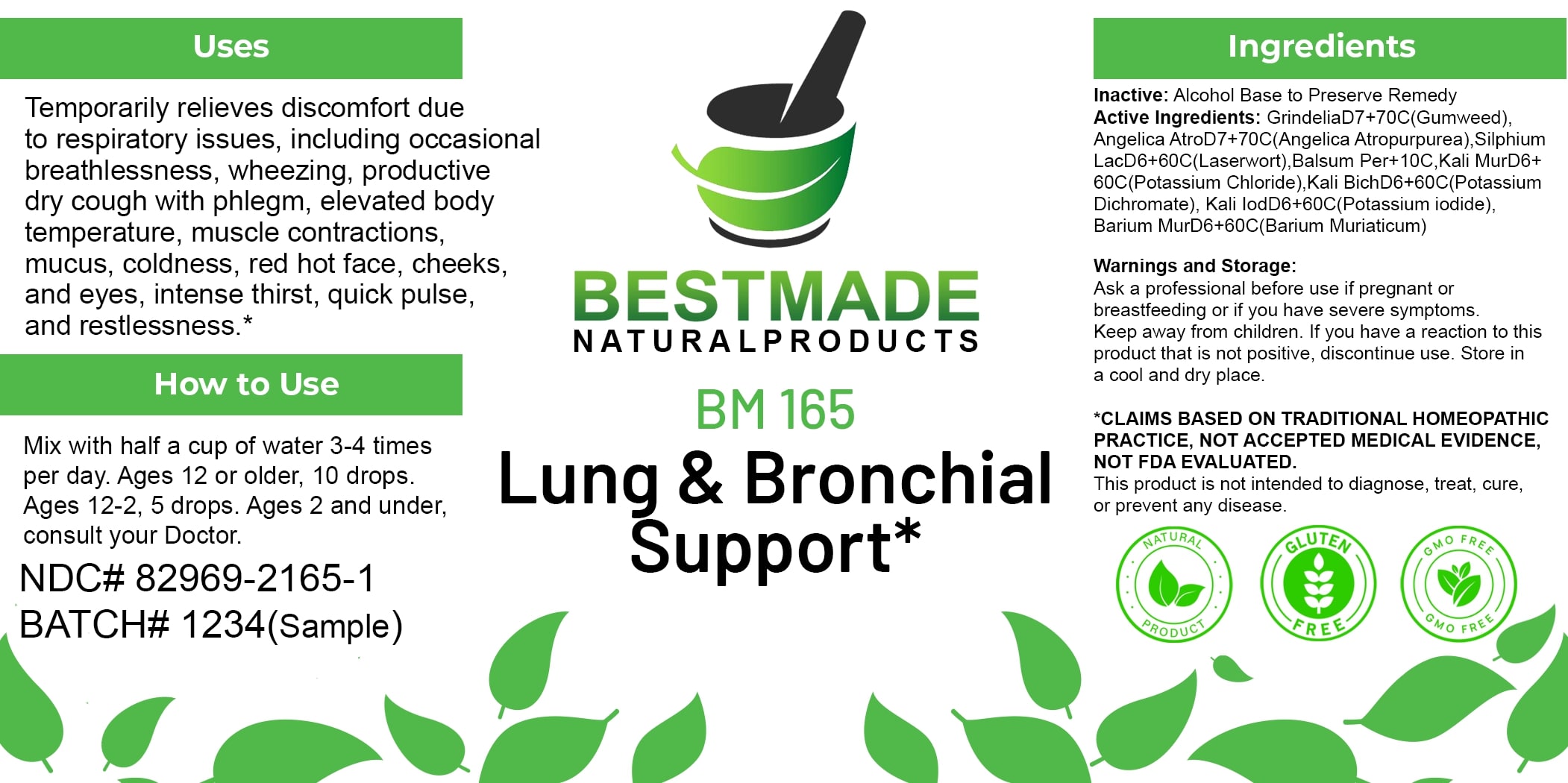 DRUG LABEL: Bestmade Natural Products BM165
NDC: 82969-2165 | Form: LIQUID
Manufacturer: Bestmade Natural Products
Category: homeopathic | Type: HUMAN OTC DRUG LABEL
Date: 20250218

ACTIVE INGREDIENTS: POTASSIUM DICHROMATE 30 [hp_C]/30 [hp_C]; GRINDELIA HIRSUTULA WHOLE 30 [hp_C]/30 [hp_C]; POTASSIUM IODIDE 30 [hp_C]/30 [hp_C]; SILPHIUM LACINIATUM 30 [hp_C]/30 [hp_C]; ANGELICA ATROPURPUREA ROOT 30 [hp_C]/30 [hp_C]; POTASSIUM CHLORIDE 30 [hp_C]/30 [hp_C]; BARIUM CHLORIDE DIHYDRATE 30 [hp_C]/30 [hp_C]; BALSAM PERU 30 [hp_C]/30 [hp_C]
INACTIVE INGREDIENTS: ALCOHOL 30 [hp_C]/30 [hp_C]

BM165

DOSAGE AND ADMINISTRATION

How to Use

Mix with half a cup of water 3-4 times per day. Ages 12 or older, 10 drops. Ages 12-2, 5 drops. Ages 2 and under, consult your Doctor.

INACTIVE INGREDIENT

Ingredients

Inactive: Alcohol Base to Preserve Remedy

ACTIVE INGREDIENT

Active Ingredients: GrindeliaD7+70C(Grindelia), Angelica AtroD7+70C(Angelica Atropurpurea), Silphium LacD6+60C(Laserwort), Balsam Per+10C, Kali MurD6+ 60C(Potassium Chloride), Kali BichD6+60C(Potassium Dichromate), Kali IodD6+60C(Potassium Iodide), Barium MurD6+60C(Barium Muriaticum)

Uses

Temporarily relieves discomfort due to respiratory issues, including occasional breathlessness, wheezing, productive dry cough with phlegm, elevated body temperature, muscle contractions, mucus, coldness, red hot face, cheeks, and eyes, intense thirst, quick pulse, and restlessness.*

*CLAIMS BASED ON TRADITIONAL HOMEOPATHIC PRACTICE, NOT ACCEPTED MEDICAL EVIDENCE. NOT FDA EVALUATED.

This product is not intended to diagnose, treat, cure, or prevent any disease.

Uses

Temporarily relieves discomfort due to respiratory issues, including occasional breathlessness, wheezing, productive dry cough with phlegm, elevated body temperature, muscle contractions, mucus, coldness, red hot face, cheeks, and eyes, intense thirst, quick pulse, and restlessness.*

*CLAIMS BASED ON TRADITIONAL HOMEOPATHIC PRACTICE, NOT ACCEPTED MEDICAL EVIDENCE. NOT FDA EVALUATED.

This product is not intended to diagnose, treat, cure, or prevent any disease.

KEEP OUT OF REACH OF CHILDREN

Warnings and Storage:

Ask a professional before use if pregnant or breastfeeding or if you have severe symptoms. Keep away from children. If you have a reaction to this product that is not positive, discontinue use. Store in a cool and dry place.

Warnings and Storage:

Ask a professional before use if pregnant or breastfeeding or if you have severe symptoms. Keep away from children. If you have a reaction to this product that is not positive, discontinue use. Store in a cool and dry place.

*CLAIMS BASED ON TRADITIONAL HOMEOPATHIC PRACTICE, NOT ACCEPTED MEDICAL EVIDENCE. NOT FDA EVALUATED.

This product is not intended to diagnose, treat, cure, or prevent any disease.

Entire package label